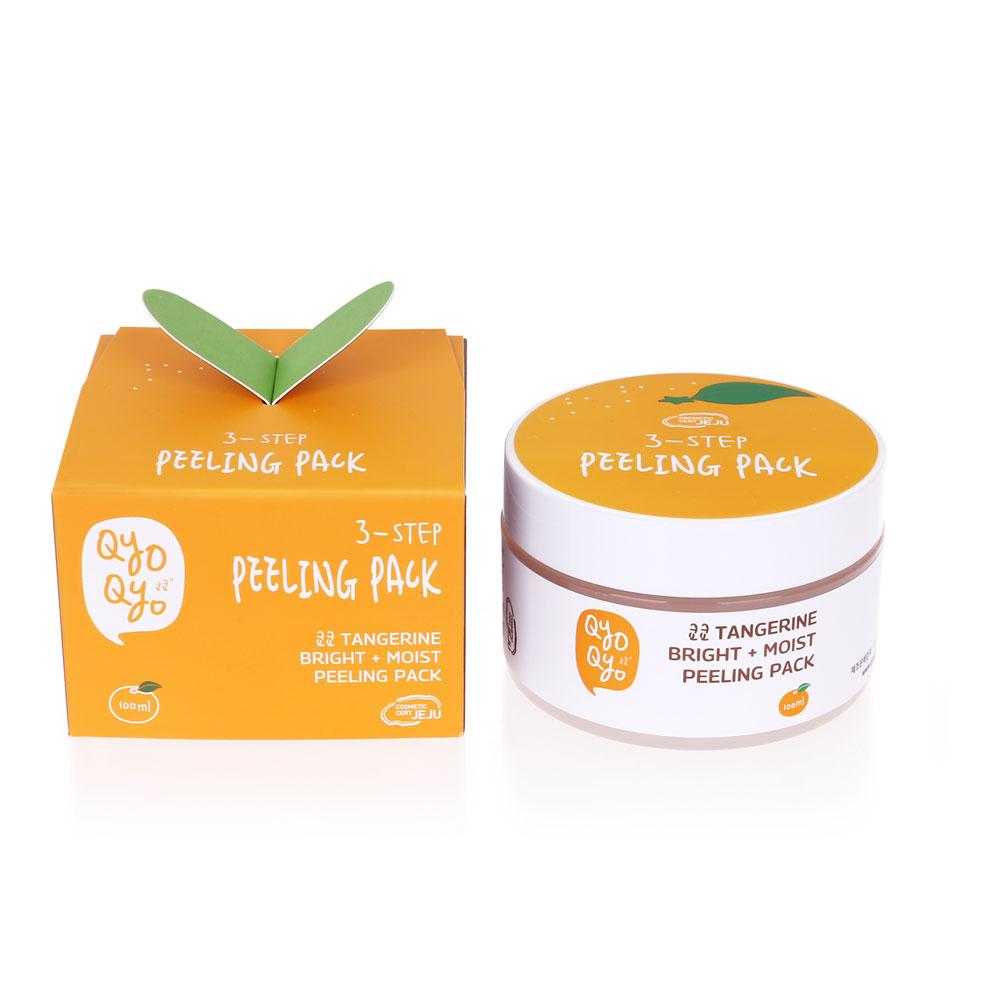 DRUG LABEL: QYO QYO Tangerine Bright Moist Peeling Pack
NDC: 71733-108 | Form: PASTE
Manufacturer: LaLa Co., Ltd.
Category: otc | Type: HUMAN OTC DRUG LABEL
Date: 20190101

ACTIVE INGREDIENTS: KAOLIN 5 g/100 mL
INACTIVE INGREDIENTS: STEARIC ACID; BUTYLENE GLYCOL; TANGERINE PEEL; WATER; GLYCERIN; BENTONITE; POTASSIUM HYDROXIDE; SODIUM LAURYL SULFATE

Qyo Qyo Tangerine Bright + Moist
Peeling Pack

ACTIVE INGREDIENTS

KAOLIN 5%

PURPOSE

SKIN PROTECTANT

USES

- Helps prevent and temporarily protects chapped or cracked skin.

WARNINGS

For external use only.

When using this product • do not get into eyes.

STOP USE

Stop us and ask doctor if • condition worsens • symptoms last
more than 7 days or clear up and occurs again within a few days.

Keep out of reach of children. If product is swallowed, get medical help or contact a Poison Control Center right away.

Directions

• Apply as needed. • After cleansing your face, apply two spatula of peeling pack and spread evenly on your face. • Wait 10 to 15 minutes. • Massage and deep cleanse your skin before rinsing with luke warm water.

Inactive Ingredients

Water, Sodium lauryl sulfate, Stearic Acid, Glycerin, Volcanic Ash, Buylene Glycol, Potassium Hydroxide, Bentonite, Betaine

Other Information

Protect this product from excessive heat and direct sun.

Questions or Comments?

Call toll free 1-800-311-6680